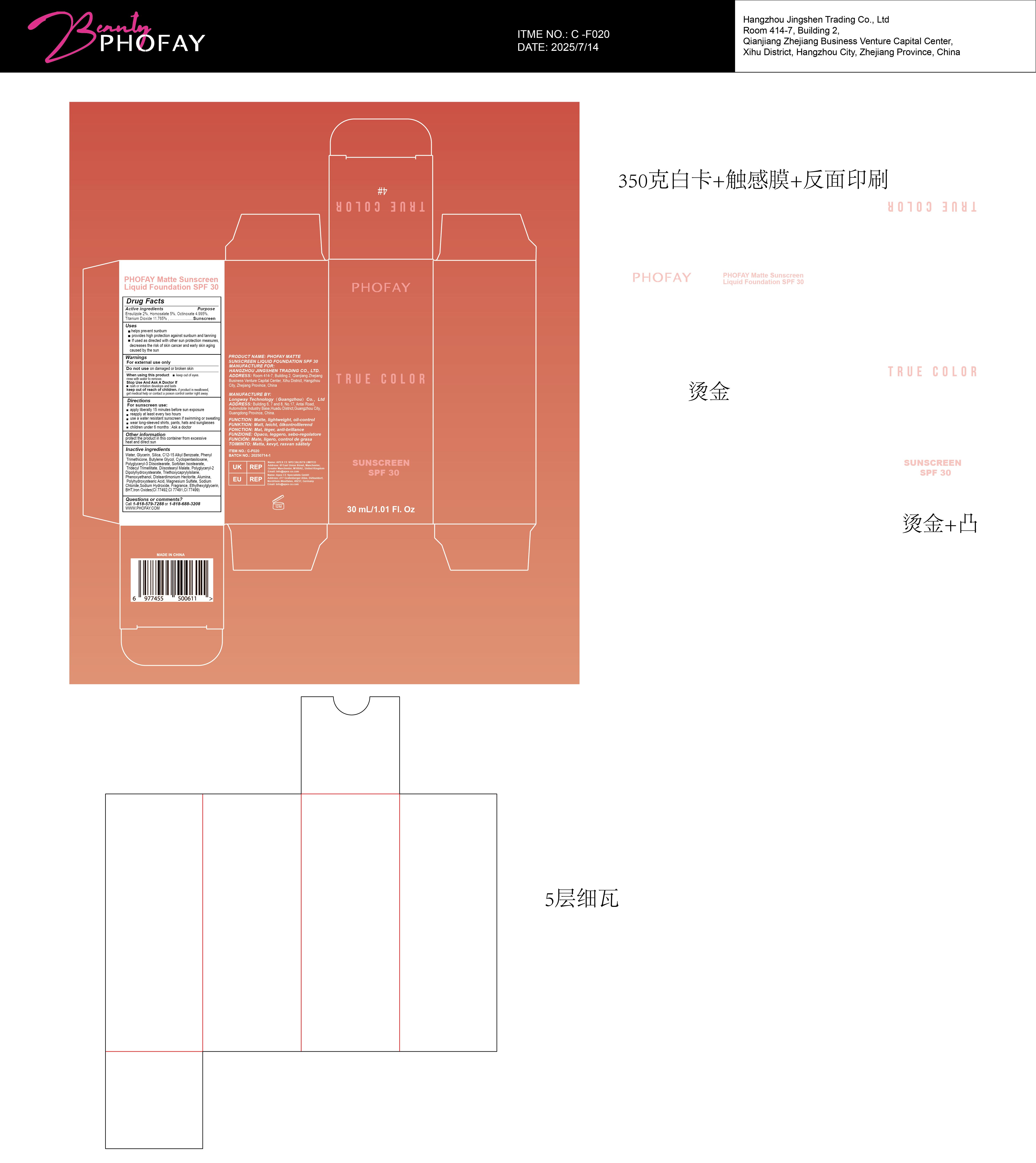 DRUG LABEL: PHOFAY Matte Sunscreen Liquid Foundation SPF 30 4
NDC: 85161-127 | Form: LOTION
Manufacturer: Longway Technology(Guangzhou) Co., Ltd.
Category: otc | Type: HUMAN OTC DRUG LABEL
Date: 20250821

ACTIVE INGREDIENTS: ENSULIZOLE 0.02 g/1 g; OCTINOXATE 0.04995 g/1 g; TITANIUM DIOXIDE 0.11765 g/1 g; HOMOSALATE 0.05 g/1 g
INACTIVE INGREDIENTS: C12-15 ALKYL BENZOATE; CYCLOPENTASILOXANE; POLYGLYCERYL-3 DIISOSTEARATE; PHENOXYETHANOL; DISTEARDIMONIUM HECTORITE; TRIETHOXYCAPRYLYLSILANE; ALUMINA; MAGNESIUM SULFATE; SODIUM HYDROXIDE; PHENYL TRIMETHICONE; WATER; ETHYLHEXYLGLYCERIN; SORBITAN ISOSTEARATE; POLYHYDROXYSTEARIC ACID (2300 MW); CI 77491; BHT; BUTYLENE GLYCOL; CI 77492; POLYGLYCERYL-2 DIPOLYHYDROXYSTEARATE; GLYCERIN; FRAGRANCE LEMON ORC2001060; SILICON DIOXIDE; CI 77499; DIISOSTEARYL MALATE; TRIDECYL TRIMELLITATE; SODIUM CHLORIDE

ACTIVE INGREDIENT

Ensulizole 2%,Homosalate 5%,Octinoxate 4.995%,Titanium Dioxide 11.765%

KEEP OUT OF REACH OF CHILDREN

if product is swallowed,get medical help or contact a poison control center right away.

WARNINGS

For external use only

Do not use on damaged or broken skin

When using this product keep out of eyes.rinse with water to remove.

Stop Use And Ask A Doctor lf

rash or irritation develops and lasts

keep out of reach of children.

if product is swallowed,get medical help or contact a poison control center right away.

DOSAGE AND ADMINISTRATION

For sunscreen use:
apply liberally 15 minutes before sun exposure

reapply at least every two hours

use a water resistant sunscreen if swimming or sweating

wear long-sleeved shirts, pants, hats and sunglasses

children under 6 months :Ask a doctor

INACTIVE INGREDIENT

Water, Glycerin,Silica, C12-15 Alkyl Benzoate, PhenylTrimethicone,Butylene Glycol, Cyclopentasiloxane,Polyglyceryl-3 Diisostearate, Sorbitan lsostearate, Tridecyl Trimellitate,Diisostearyl Malate,Polyglyceryl-2 Dipolyhydroxystearate, Triethoxycaprylylsilane, Phenoxyethanol,Disteardimonium Hectorite,Alumina, Polyhydroxystearic Acid, Magnesium Sulfate, Sodium Chloride,Sodium Hydroxide, Fragrance, Ethylhexylglycerin, BHT,lron Oxides(Cl77492,C177491,C177499)

OTHER SAFETY INFORMATION

protect the product in this container from excessive

heat and direct sun

PURPOSE

Suncreen

INDICATIONS AND USAGE

helps prevent sunburn

provides high protection against sunburn and tanning

lf used as directed with other sun protection measures.

decreases the risk of skin cancer and early skin aging caused by the sun